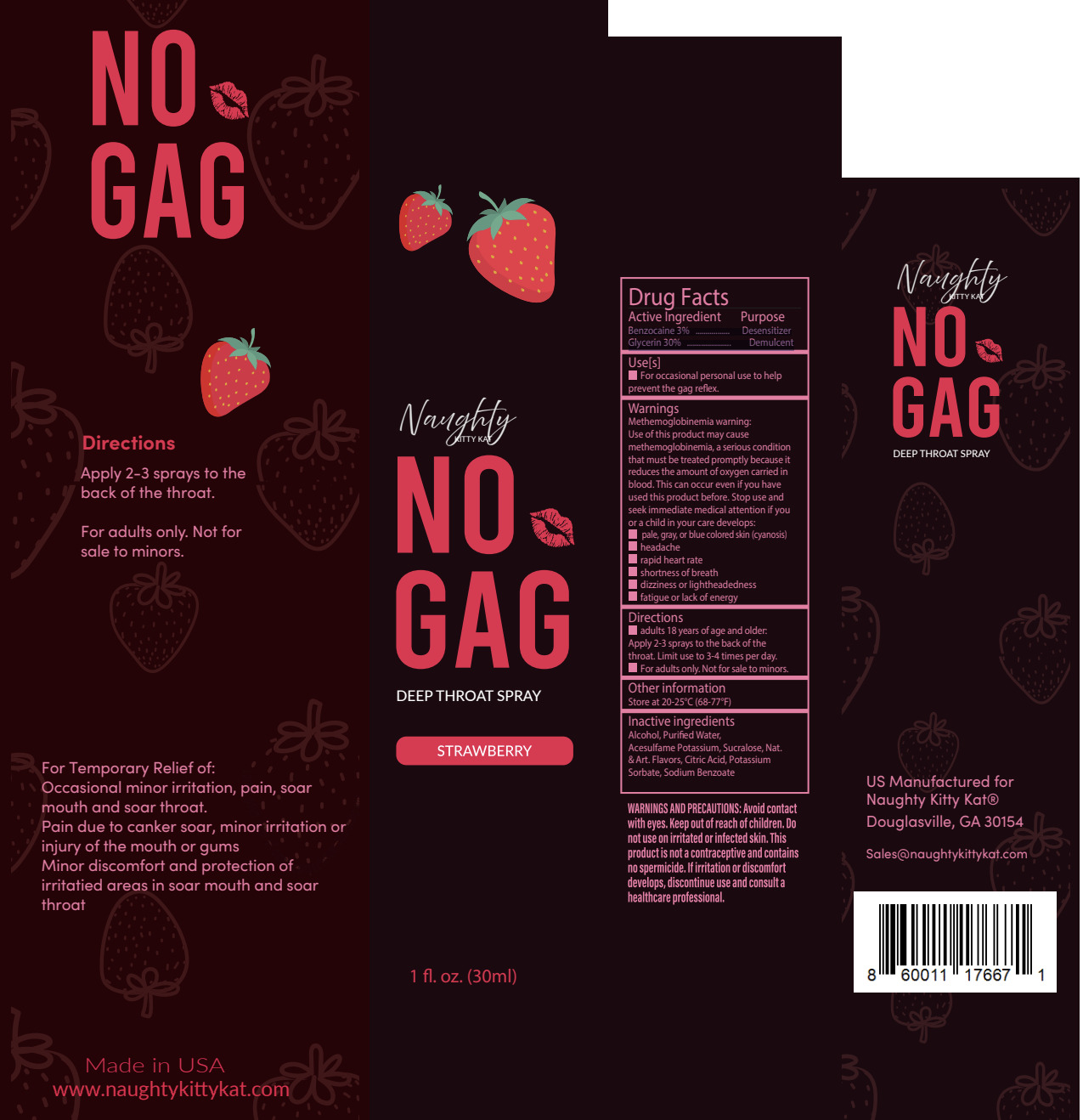 DRUG LABEL: Naughty Kitty Kat
NDC: 84243-211 | Form: SPRAY
Manufacturer: INKED SUGAR, INC
Category: otc | Type: HUMAN OTC DRUG LABEL
Date: 20251219

ACTIVE INGREDIENTS: BENZOCAINE 3 mg/100 mL; GLYCERIN 30 mg/100 mL
INACTIVE INGREDIENTS: WATER; SUCRALOSE; ACESULFAME POTASSIUM; ALCOHOL; CITRIC ACID MONOHYDRATE; SODIUM BENZOATE; POTASSIUM SORBATE

INKED-PLP Naughty Kitty Kat

Active Ingredient(s)

Benzocaine 3% ................. Desensitizer Glycerin 30% ...................... Demulcent

Purpose

Desensitizer Demulcent

Use

For occasional personal use to help prevent the gag reflex

Warnings

Methemoglobinemia warning:

Use of this product may cause methemoglobinemia, a serious condition that must be treated promptly because it reduces the amount of oxygen carried in the blood. This can occur even if you have used this product before. Stop use and seek immediate medical attention if you or a child in your care develops pale, gray, or blue-colored skin (cyanosis), headache rapid heart rate, shortness of breath, dizziness or lightheadedness, fatigue or lack of energy

This product is not a contraceptive and contains no spermicide.

WHEN USING

Avoid contact with the eyes. Do not use an irritated or infected skin.

Keep away from children.

STOP USE

adults 18 years of age and older: Apply 2-3 sprays to the back of the throat. Limit use to 3-4 times per day. For adults only. Not for sale to minors.

Directions

Adults: Before applying this product, gently dry the application area by patting or blotting it with toilet tissue or a clean, soft cloth.

Apply up to 6 times daily. Children under 12 years: consult a doctor.

Other information

Store at 20-25°C (68-77°F)

Inactive ingredients

Alcohol, Purifi ed Water, Acesulfame Potassium, Sucralose, Nat. & Art. Flavors, Citric Acid, Potassium Sorbate, Sodium Benzoate

Package Label - Principal Display Panel

30mL NDC: 84243-211-11